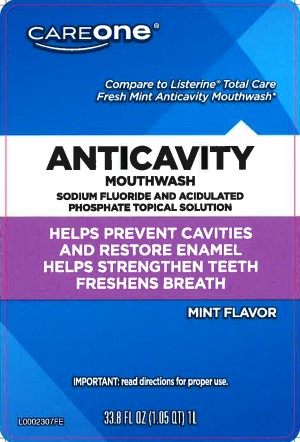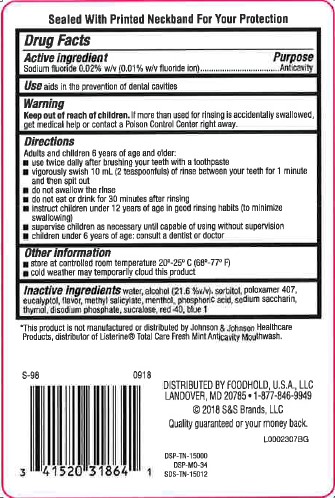 DRUG LABEL: Anticavity
NDC: 72476-005 | Form: MOUTHWASH
Manufacturer: Retail Business Services, LLC 
Category: otc | Type: HUMAN OTC DRUG LABEL
Date: 20260206

ACTIVE INGREDIENTS: SODIUM FLUORIDE 0.1 mg/1 mL
INACTIVE INGREDIENTS: WATER; ALCOHOL; SORBITOL; POLOXAMER 407; EUCALYPTOL; METHYL SALICYLATE; MENTHOL; PHOSPHORIC ACID; SACCHARIN SODIUM; THYMOL; SODIUM PHOSPHATE, DIBASIC, ANHYDROUS; SUCRALOSE; FD&C RED NO. 40; FD&C BLUE NO. 1

Care One 163.004/163AE
Anticavity Fluoride Mouthrinse

Tamper Evident Statement

Sealed With Printed Neckband For Your Protection

Active ingredient

Sodium fluoride 0.02% w/v (0.01%w/v fluoride ion)

Purpose

Anticavity

Use

aids in the prevention of dental cavities

Warnings

for this product

Keep out of reach of children.

If more than used for rinsing is accidentally swallowed, get medical help or contact a Poison Control Center right away.

Directions

Adults and children 12 years of age and older:

- use twice daily after brushing your teeth with a toothpaste
- vigorously swish 10 mL (2 teaspoonfuls) of rinse between your teeth for 1 minute and then spit out
- do not swallow the rinse
- do not eat or drink for 30 minutes after rinsing
- instruct children under 12 of age in good rinsing habits (to minimize swallowing)
- supervise children as necessary until capable of using without supervision
- children under 12 years of age: consult a dentist or doctor

Other information

- store at controlled room temperature 20⁰ -25⁰ (68⁰ - 77⁰ F)
- cold weather may temporarily cloud this product

Inactive ingredients

water, alcohol (21.6 %v/v), sorbitol, poloxamer 407, eucalyptol, flavor, methyl salicylate, menthol, phosphoric acid, sodium saccharin, thymol, disodium phosphate, sucralose, red 40, blue 1

Disclaimer

*This product is not manufactured or distributed by Johnson & Johnson Healthcare Products, distributor of Listerine®Total Care Fresh Mint Anticavity Mouthwash.

ADVERSE REACTION

DISTRIBUTED BY:

FOODHOLD U.S.A., LLC

LANDOVER, MD 20785

1-877-846-9949

©2018 S&S BRANDS, LLC

Quality guaranteed or your money back

DSP-TN-15000

DSP-MO-34

SDS-TN-15012

Principal display panel

CARE ONE®

Compare to Listerine®Total Care Fresh Mint Anticavity Mouthwash*

ANTICAVITY

MOUTHWASH

SODIUM FLUORIDE & ACIDULATED PHOSPHATE TOPICAL SOLUTION

Helps prevent cavities and restore enamel

Helps strengthen teeth

Freshens breath

Mint Flavor

IMPORTANT: Read directions for proper use.

33.8 FL OZ (1.05 QT) 1 L